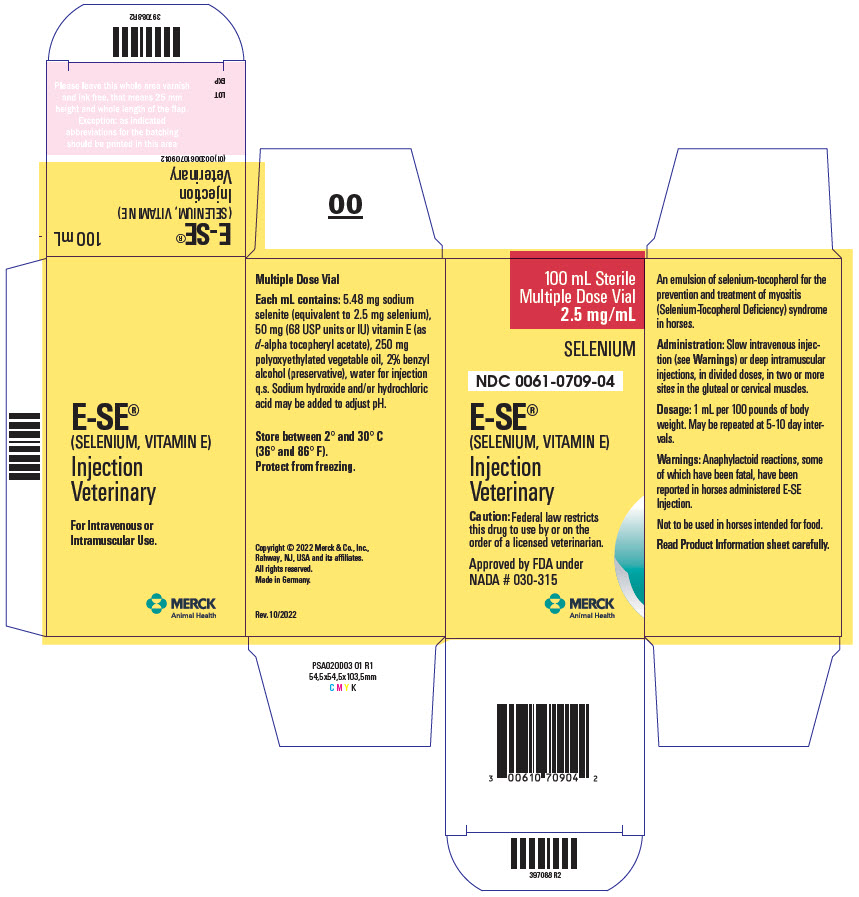 DRUG LABEL: E-SE
NDC: 0061-0709 | Form: INJECTION, SOLUTION
Manufacturer: Schering Corporation
Category: animal | Type: PRESCRIPTION ANIMAL DRUG LABEL
Date: 20241112

ACTIVE INGREDIENTS: SODIUM SELENITE 2.5 mg/1 mL; .ALPHA.-TOCOPHEROL ACETATE, D- 68 [USP'U]/1 mL
INACTIVE INGREDIENTS: WATER

E-SE®
(SELENIUM, VITAMIN E)
Injection

FOR VETERINARY USE ONLY

Approved by FDA under NADA # 030-315

PRODUCT INFORMATION

CAUTION Federal law restricts this drug to use by or on the order of a licensed veterinarian.

DESCRIPTION

DESCRIPTION E-SE Injection is an emulsion of selenium-tocopherol for the prevention and treatment of myositis (Selenium-Tocopherol Deficiency) syndrome in horses. Each mL contains: 5.48 mg sodium selenite (equivalent to 2.5 mg selenium), 50 mg (68 USP units or IU) vitamin E (as d-alpha tocopheryl acetate), 250 mg polyoxyethylated vegetable oil, 2% benzyl alcohol (preservative), water for injection q.s. Sodium hydroxide and/or hydrochloric acid may be added to adjust pH.

CLINICAL PHARMACOLOGY

PHARMACOLOGY It has been demonstrated that selenium and tocopherol exert physiological effects and that these effects are intertwined with sulfur metabolism. Additionally, tocopherol appears to have a significant role in the oxidation process, thus suggesting an interrelationship between selenium and tocopherol in overcoming sulfur-induced depletion and restoring normal metabolism. Although oral ingestion of adequate amounts of selenium and tocopherol would seemingly restore normal metabolism, it is apparent that the presence of sulfur and, perhaps, other factors interfere during the digestive process with proper utilization of selenium and tocopherol. When selenium and tocopherol are injected, they bypass the digestive process and exert their full metabolic effects promptly on cell metabolism. Anti-inflammatory action has been demonstrated by selenium-tocopherol in the Selye Pouch Technique and experimentally induced polyarthritis study in rats.

VETERINARY INDICATIONS

INDICATIONS E-SE Injection is recommended for the control of the following clinical signs when associated with myositis (Selenium-Tocopherol Deficiency) syndrome: rapid respiration, profuse sweating, muscle spasms and stiffness, elevated SGOT.

CAUTION Intravenous administration, if elected, should be by slow injection.

Emulsions injected intramuscularly into the horse may produce transitory local muscle soreness and can be prevented to some degree by injecting deeply (2 to 21/2 inches), in divided doses, in two or more sites. Do not continue therapy in horses demonstrating such sensitivity.

Selenium is toxic if administered in excess. A fixed dose schedule is therefore important (read package insert for each selenium-tocopherol product carefully before using).

WARNINGS

WARNINGS Anaphylactoid reactions, some of which have been fatal, have been reported in horses administered E-SE Injection. Signs include excitement, sweating, trembling, ataxia, respiratory distress, and cardiac dysfunction. These reactions have been reported as associated both with intravenous and intramuscular injections. It is presently unknown whether the mode of application affects the frequency of such reactions. However, reactions associated with intramuscular injections have been reported to manifest more slowly and hence may give more time to institute treatment for anaphylaxis, such as epinephrine and/or corticosteroid injection.

Medications which have been reported to cause major adverse reactions in horses should be avoided when E-SE is administered, unless the condition of the animal requires such use.

Not to be used in horses intended for food.

DOSAGE AND ADMINISTRATION Administration: slow intravenous injection (see WARNINGS) or deep intramuscular injections, in divided doses, in two or more sites in the gluteal or cervical muscles. Dosage: 1 mL per 100 pounds of body weight. May be repeated at 5-10 day intervals.

PRECAUTIONS

PRECAUTIONS Selenium-Tocopherol Deficiency (STD) syndrome produces a variety and complexity of symptoms often interfering with a proper diagnosis. Even in selenium deficient areas there are other disease conditions which produce similar clinical signs. It is imperative that all these conditions be carefully considered prior to treatment of STD syndrome. Serum selenium levels, elevated SGOT, and creatine levels may serve as aids in arriving at a diagnosis of STD, when associated with other indices.

Important Use only the selenium-tocopherol product recommended for each species. Each formulation is designed for the species indicated to produce the maximum efficacy and safety.

HOW SUPPLIED

HOW SUPPLIED 100 mL sterile, multiple-dose glass vial, NDC 0061-0709-04.

STORAGE AND HANDLING

STORAGE Store between 2 and 30 C (36 and 86 F). Protect from freezing.

Rev. 10-2022

Copyright © 2022 Merck & Co., Inc., Rahway,
NJ, USA and its affiliates.
All rights reserved.
Made in Germany.

MERCK
Animal Health

399371 R2

PRINCIPAL DISPLAY PANEL - 100 mL Vial Carton

100 mL Sterile
Multiple Dose Vial
2.5 mg/mL

SELENIUM

NDC 0061-0709-04

E-SE®
(SELENIUM, VITAMIN E)

Injection
Veterinary

Caution: Federal law restricts
this drug to use by or on the
order of a licensed veterinarian.

Approved by FDA under
NADA # 030-315

MERCK
Animal Health